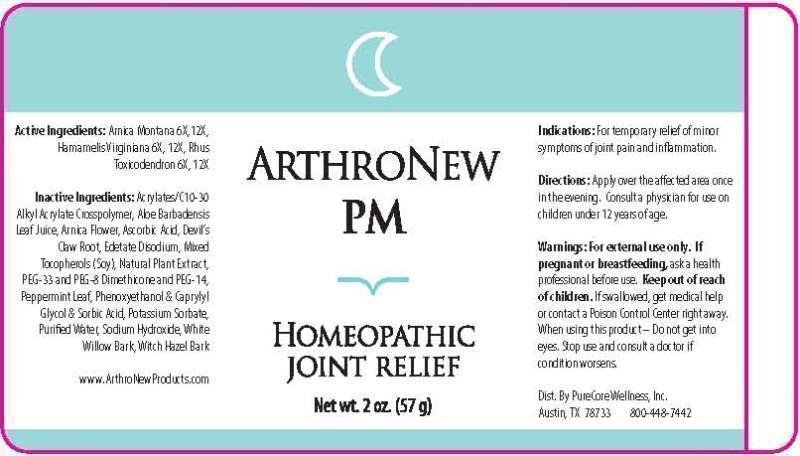 DRUG LABEL: ARTHRONEW
NDC: 61045-0002 | Form: GEL
Manufacturer: PureCore Wellness, Inc
Category: homeopathic | Type: HUMAN OTC DRUG LABEL
Date: 20141106

ACTIVE INGREDIENTS: ARNICA MONTANA 6 [hp_X]/1 g; HAMAMELIS VIRGINIANA ROOT BARK/STEM BARK 6 [hp_X]/1 g; TOXICODENDRON PUBESCENS LEAF 6 [hp_X]/1 g
INACTIVE INGREDIENTS: CARBOMER COPOLYMER TYPE A (ALLYL PENTAERYTHRITOL CROSSLINKED); ALOE VERA LEAF; ARNICA MONTANA FLOWER; ASCORBIC ACID; HARPAGOPHYTUM PROCUMBENS ROOT; EDETATE DISODIUM; .ALPHA.-TOCOPHEROL; OREGANO; POLYETHYLENE GLYCOL 1500; PEG-8 DIMETHICONE; POLYETHYLENE GLYCOL 700; MENTHA PIPERITA LEAF; PHENOXYETHANOL; CAPRYLYL GLYCOL; SORBIC ACID; POTASSIUM SORBATE; WATER; SODIUM HYDROXIDE; SALIX ALBA BARK; HAMAMELIS VIRGINIANA BARK

DRUG FACTS:

ACTIVE INGREDIENTS:

ARNICA MONTANA 6X, 12X, HAMAMELIS VIRGINIANA 6X, 12X, RHUS TOXICODENDRON 6X, 12X

INDICATIONS:

For temporary relief of minor symptoms of joint pain and inflammation.

WARNINGS:

For external use only. If pregnant or breastfeeding, ask a health professional before use.

Keep out of reach of children. If swallowed, get medical help or contact a Poison Control Center right away.

When using this product - Do not get into eyes. Stop use and consult a doctor if condition worsens.

Keep out of reach of children. If swallowed, get medical help or contact a Poison Control Center right away.

DIRECTIONS:

Apply over the affected area once in the evening. Consult a physician for use in children under 12 years of age.

INDICATIONS:

For temporary relief of minor symptoms of joint pain and inflammation.

INACTIVE INGREDIENTS:

ACRYLATES/C10-30 ALKYL ACRYLATE CROSSPOLYMER, ALOE BARBADENSIS LEAF JUICE, ARNICA (FLOWER), ASCORBIC ACID, DEVIL'S CLAW (ROOT), EDETATE DISODIUM (EDTA), MIXED TOCOPHEROLS [VITAMIN E] (DERIVED FROM SOY BEAN), NATURAL PLANT EXTRACT, PEG-33, PEG-8 DIMETHICONE, PEG-14, PEPPERMINT (LEAF), PHENOXYETHANOL, CAPRYLYL GLYCOL, SORBIC ACID, POTASSIUM SORBATE, PURIFIED WATER, SODIUM HYDROXIDE, WHITE WILLOW (BARK), WITCH HAZEL (BARK)

QUESTIONS:

Dist. By

PureCore Wellness, Inc.

Austin, TX 78733

800-448-7442

www.ArthroNewProducts.com

PACKAGE LABEL DISPLAY:

ARTHRONEW

PM

HOMEOPATHIC

JOINT RELIEF

Net wt. 2 oz. (57 g)